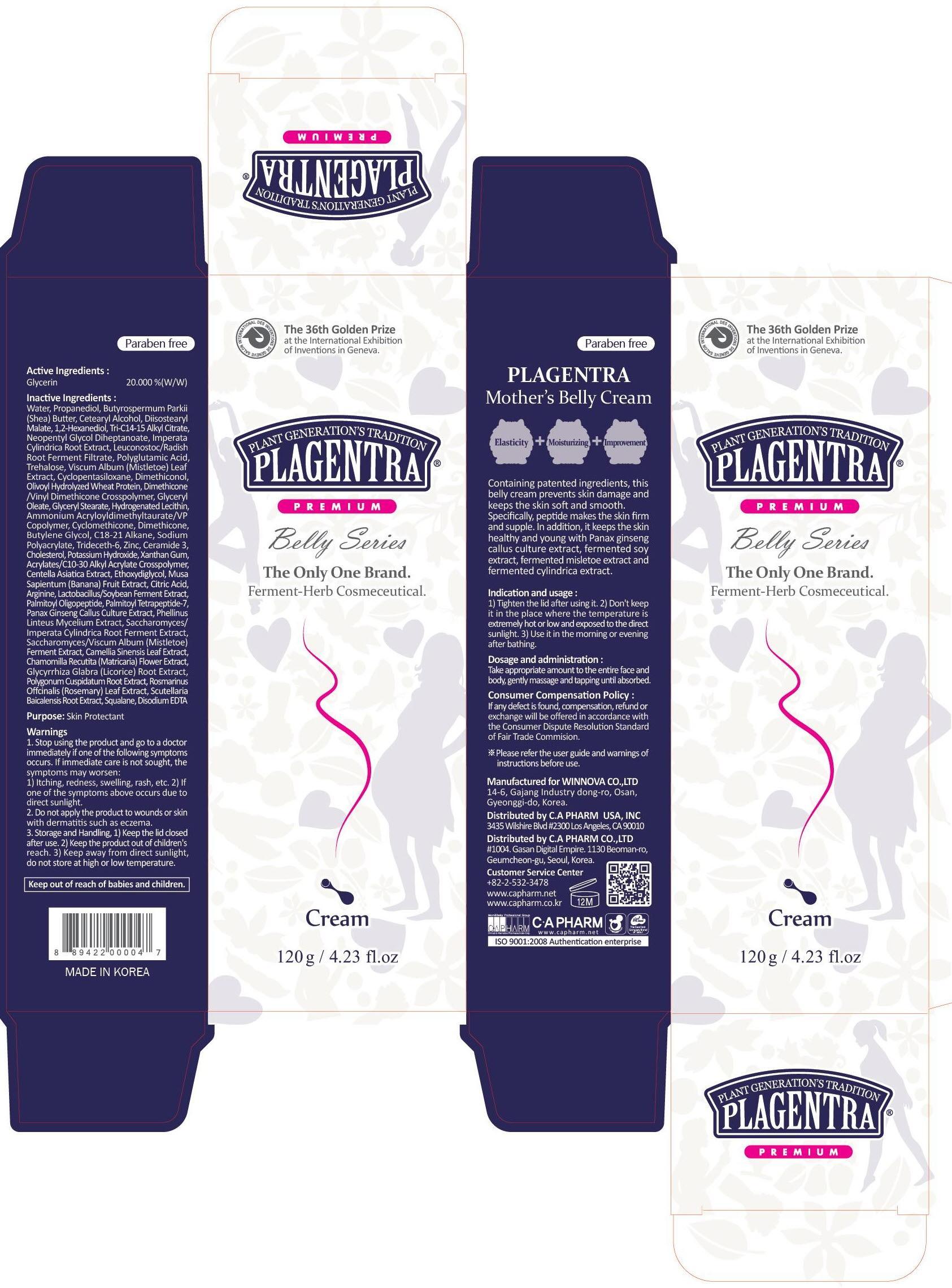 DRUG LABEL: PLAGENTRA MOTHERS BELLY
NDC: 68988-020 | Form: CREAM
Manufacturer: C.A Pharm Co., Ltd.
Category: otc | Type: HUMAN OTC DRUG LABEL
Date: 20141205

ACTIVE INGREDIENTS: Glycerin 24 g/120 g
INACTIVE INGREDIENTS: Water; Propanediol

ACTIVE INGREDIENT

Active Ingredient: Glycerin 20%

INACTIVE INGREDIENT

Inactive Ingredients:
Water, Propanediol, Butyrospermum Parkii (Shea) Butter, Cetearyl Alcohol, Diisostearyl Malate, 1,2-Hexanediol, Tri-C14-15 Alkyl Citrate, Neopentyl Glycol Diheptanoate, Imperata Cylindrica Root Extract, Leuconostoc/Radish Root Ferment Filtrate, Polyglutamic Acid, Trehalose, Viscum Album (Mistletoe) Leaf Extract, Cyclopentasiloxane, Dimethiconol, Olivoyl Hydrolyzed Wheat Protein, Dimethicone/Vinyl Dimethicone Crosspolymer, Glyceryl Oleate, Glyceryl Stearate, Hydrogenated Lecithin, Ammonium Acryloyldimethyltaurate/VP Copolymer, Cyclomethicone, Dimethicone, Butylene Glycol, C18-21 Alkane, Sodium Polyacrylate, Trideceth-6, Zinc, Ceramide 3, Cholesterol, Potassium Hydroxide, Xanthan Gum, Acrylates/C10-30 Alkyl Acrylate Crosspolymer, Centella Asiatica Extract, Ethoxydiglycol, Musa Sapientum (Banana) Fruit Extract, Citric Acid, Arginine, Lactobacillus/Soybean Ferment Extract, Palmitoyl Oligopeptide, Palmitoyl Tetrapeptide-7, Panax Ginseng Callus Culture Extract, Phellinus Linteus Mycelium Extract, Saccharomyces/Imperata Cylindrica Root Ferment Extract, Saccharomyces/Viscum Album (Mistletoe) Ferment Extract, Camellia Sinensis Leaf Extract, Chamomilla Recutita (Matricaria) Flower Extract, Glycyrrhiza Glabra (Licorice) Root Extract, Polygonum Cuspidatum Root Extract, Rosmarinus Offcinalis (Rosemary) Leaf Extract, Scutellaria Baicalensis Root Extract, Squalane, Disodium EDTA

PURPOSE

Purpose: Skin Protectant

WARNINGS

1. Stop using the product and go to a doctor immediately if one of the following symptoms occurs. If immediate care is not sought, the symptoms may worsen :
1) Itching, redness, swelling, rash, etc. 2) If one of the symptoms above occurs due to direct sunlight.
2. Do not apply the product to wounds or skin with dermatitis such as eczema.
3. Storage and Handling, 1) Keep the lid closed after use. 2) Keep the product out of children's reach. 3) Keep away from direct sunlight, do not store at high or low temperature.

KEEP OUT OF REACH OF CHILDREN

Keep out of reach of babies and children

INDICATIONS & USAGE

Indication and usage:
1) Tighten the lid after using it. 2) Don't keep it in the place where the temperature is extremely hot or low and exposed to the direct sunlight. 3) Use it in the morning or evening after shower.

DOSAGE & ADMINISTRATION

Dosage and administration:
Take appropriate amount to the entire face and body, gently massage and tapping until absorbed.